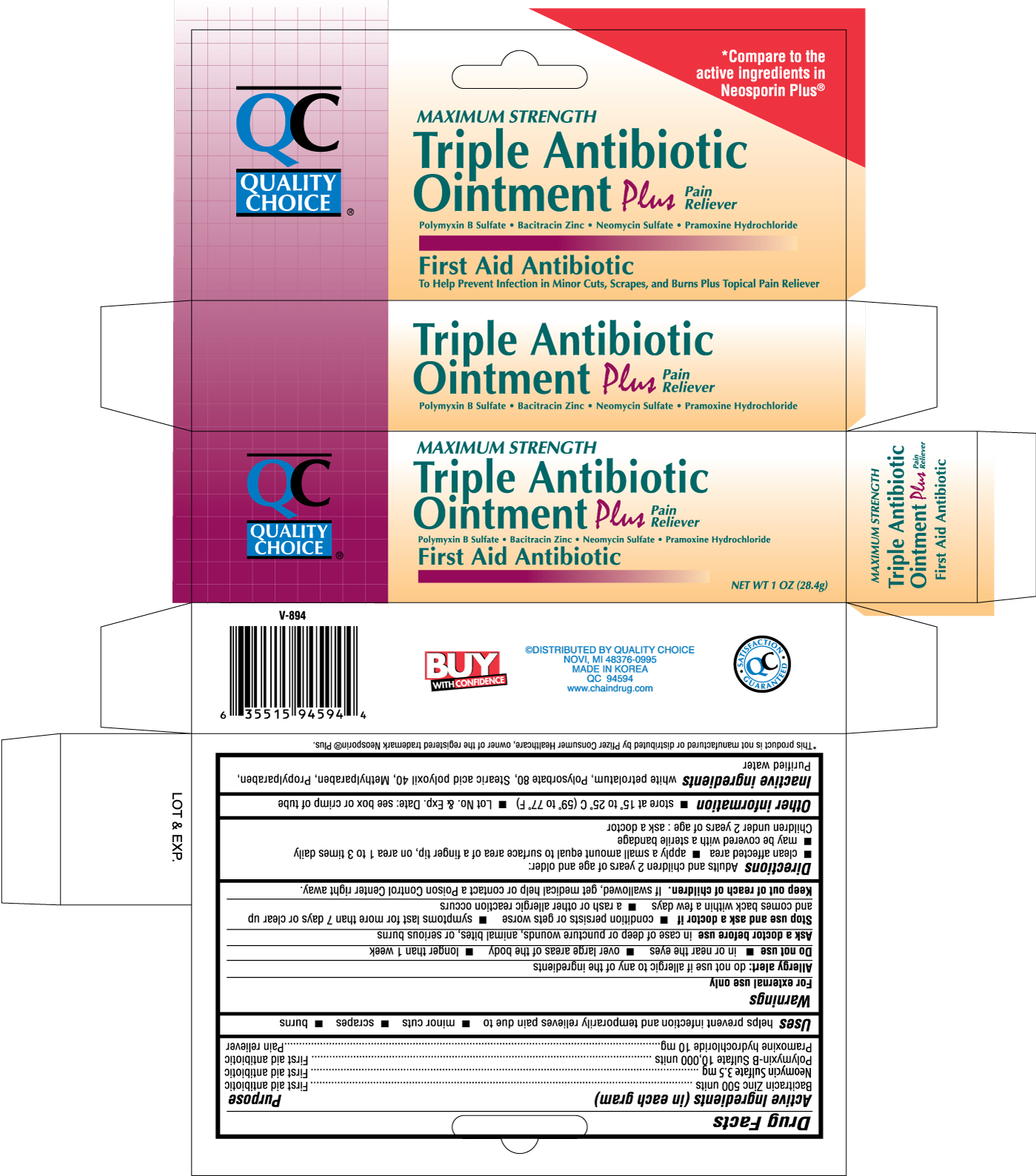 DRUG LABEL: QUALITY CHOICE TRIPLE ANTIBIOTIC PLUS PAIN RELIEVER
NDC: 63868-945 | Form: OINTMENT
Manufacturer: CHAIN DRUG MARKETING ASSOCIATION INC
Category: otc | Type: HUMAN OTC DRUG LABEL
Date: 20120209

ACTIVE INGREDIENTS: BACITRACIN ZINC 500 [USP'U]/1 g; NEOMYCIN SULFATE 3.5 mg/1 g; POLYMYXIN B SULFATE 10000 [USP'U]/1 g; PRAMOXINE HYDROCHLORIDE 10 mg/1 g
INACTIVE INGREDIENTS: PETROLATUM; POLYSORBATE 80; METHYLPARABEN; PROPYLPARABEN; WATER

Drug Facts

Uses

help prevent infection and temporarily relieves pain due to

- minor cuts
- scrapes
- burns

Warnings

For external use only

Allergy alert: do not use if allergic to any of the ingredients

Do not use

- in or near the eyes
- over large areas of the body
- longer than 1 week

Ask a doctor before use in case of deep or puncture wounds, animal bites, or serious burns

Stop use and ask a doctor if

- condition persists or gets worse
- symptoms last for more than 7 days or clear up and comes back within a few days
- a rash or other allergic reaction occurs

Keep out of reach of children. If swallowed, get medical help or contact a Poison Control Center right away.

Directions

Adults and children 2 years and older:

- clean affected area
- apply a small amount (equal to the surface area of the tip of a finger) on area 1 to 3 times daily

- may be covered with a sterile bandage

Children under 2 years: ask a doctor

Other information

- store at 15o to 25o C (59o to 77o F)
- Lot No. and Exp. Date: see box or crimp of tube

Inactive ingredients

white petrolatum, Polysorbate 80, Stearic acid polyoxil 40, Methylparaben, Propylparaben, Purified Water

DOSAGE AND ADMINISTRATION

Distributed By Quality Choice

NOVI, MI 48376-0995

MADE IN KOREA

QC 94594

www.chaindrug.com

PACKAGE LABEL

Enter section text here

Active Ingredients (in each gram) Purpose

Bacitracin Zinc 500 units .................................................................................First aid antibiotic

Neomycin Sulfate 3.5 mg.................................................................................First aid antibiotic

Polymyxin-B Sulfate 10,000 units.....................................................................First aid antibiotic

Pramoxine hydrochloride 10 mg........................................................................Pain reliever